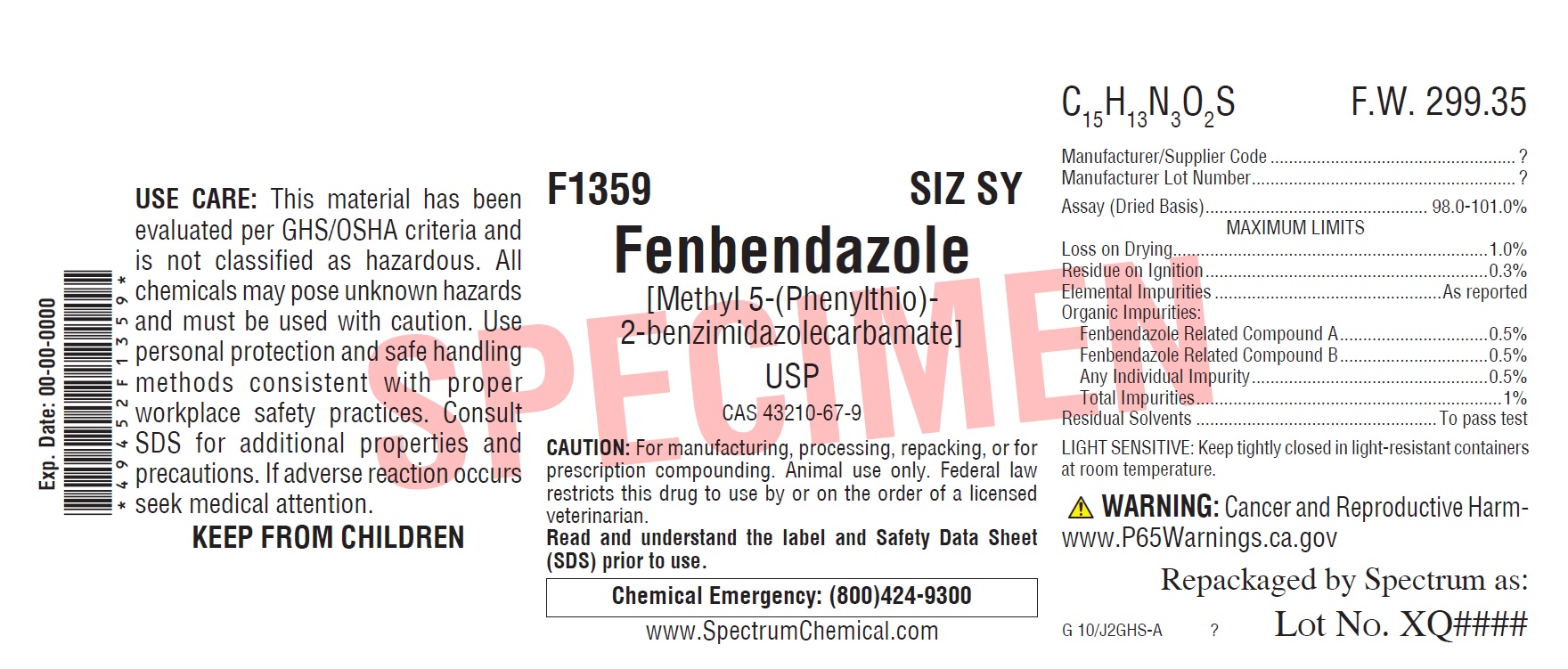 DRUG LABEL: Fenbendazole
NDC: 49452-3035 | Form: POWDER
Manufacturer: Spectrum Laboratory Products, Inc.
Category: other | Type: BULK INGREDIENT
Date: 20210126

ACTIVE INGREDIENTS: FENBENDAZOLE 1 g/1 g

Fenbendazole, USP